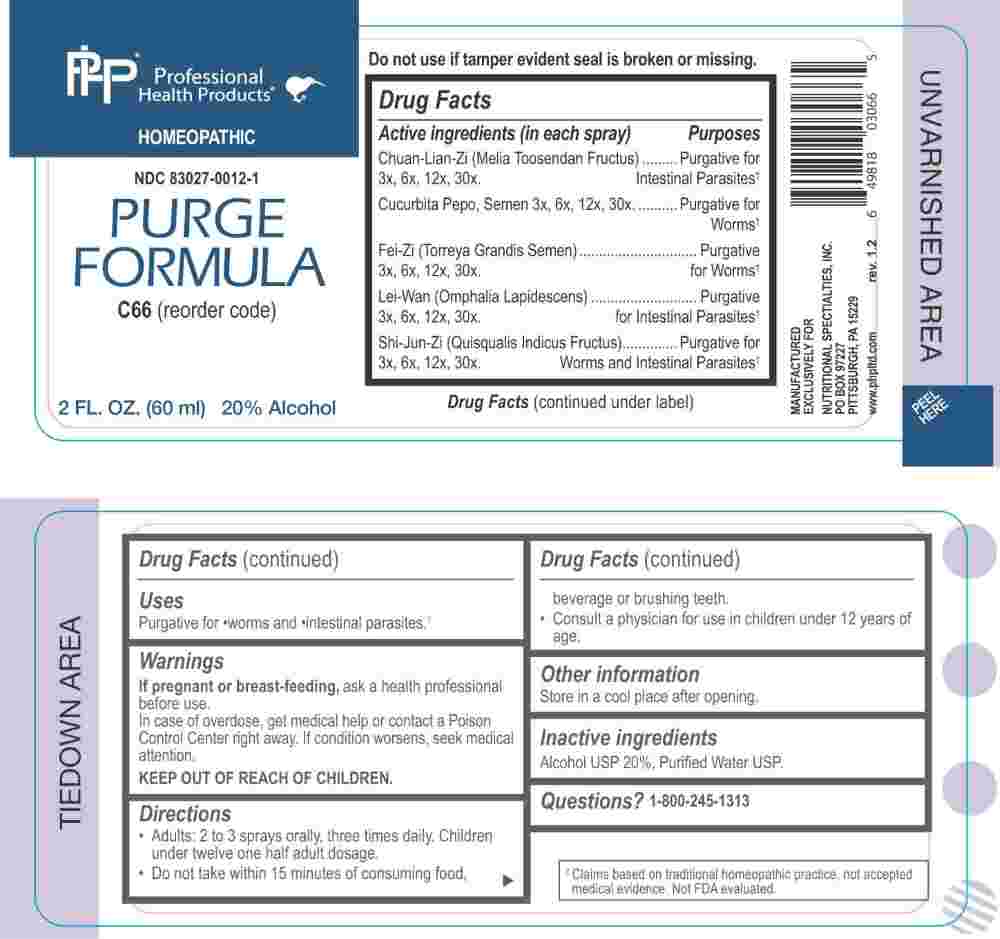 DRUG LABEL: Purge Formula
NDC: 83027-0012 | Form: SPRAY
Manufacturer: Nutritional Specialties, Inc.
Category: homeopathic | Type: HUMAN OTC DRUG LABEL
Date: 20250407

ACTIVE INGREDIENTS: MELIA AZEDARACH FRUIT 3 [hp_X]/1 mL; PUMPKIN SEED 3 [hp_X]/1 mL; TORREYA GRANDIS SEED 3 [hp_X]/1 mL; HONEY MUSHROOM 3 [hp_X]/1 mL; QUISQUALIS INDICA FRUIT 3 [hp_X]/1 mL
INACTIVE INGREDIENTS: WATER; ALCOHOL

DRUG FACTS:

ACTIVE INGREDIENTS:

Chuan-Lian-Zi (Melia Toosendan Fructus) 3X, 6X, 12X, 30X, Cucurbita Pepo, Semen 3X, 6X, 12X, 30X, Fei-Zi (Torreya Grandis Semen) 3X, 6X, 12X, 30X, Lei-Wan (Omphalia Lapidescens) 3X, 6X, 12X, 30X, Shi-Jun-Zi (Quisqualis Indicus Fructus) 3X, 6X, 12X, 30X.

PURPOSE:

Chuan-Lian-Zi (Melia Toosendan Fructus) – Purgative for intestinal Parasites,† Cucurbita Pepo, Semen – Purgative for Worms,† Fei-Zi (Torreya Grandis Semen) – Purgative for Worms,† Lei-Wan (Omphalia Lapidescens) – Purgative for Intestinal Parasites,† Shi-Jun-Zi (Quisqualis Indicus Fructus – Purgative for Worms and Intestinal Parasites†

†Claims based on traditional homeopathic practice, not accepted medical evidence. Not FDA Evaluated.

USES:

Purgative for •worms and •intestinal parasites.

WARNINGS:

If pregnant or breast-feeding, ask a health professional before use.

In case of overdose, get medical help or contact a Poison Control Center right away.

If condition worsens, seek medical attention.

KEEP OUT OF REACH OF CHILDREN

Do not use if tamper evident seal is broken or missing.

Store in a cool place after opening

KEEP OUT OF REACH OF CHILDREN:

In case of overdose, get medical help or contact a Poison Control Center right away.

DIRECTIONS:

• Adults: 2 to 3 sprays orally, three times daily. Children under twelve one half adult dosage.

• Do not take within 15 minutes of consuming food, beverage or brushing teeth.

Consult a physician for use in children under 12 years of age.

INACTIVE INGREDIENTS:

Alcohol USP 20%, Purified Water USP.

QUESTIONS:

MANUFACTURED EXCLUSIVELY FOR

NUTRITIONAL SPECIALTIES, INC.

PO BOX 97227

PITTSBURG, PA 15229

www.phpltd.com

1-800-245-1313

PACKAGE LABEL DISPLAY:

Professional

Health Products

HOMEOPATHIC

NDC 83027-0012-1

PURGE

FORMULA

2 FL. OZ (60 ml)